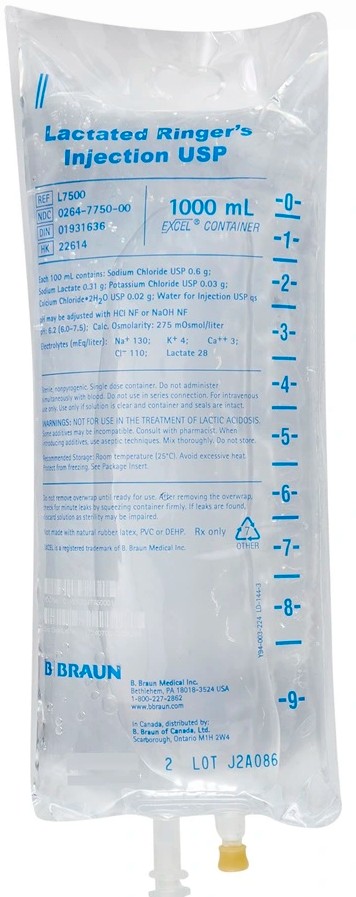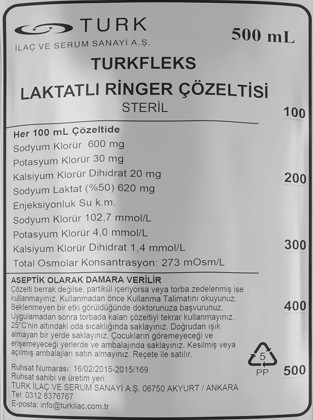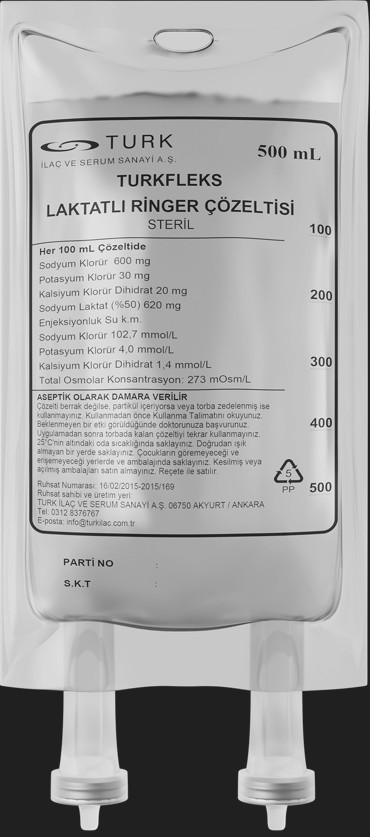 DRUG LABEL: Turkfleks Lactated Ringer Solution
NDC: 85160-500 | Form: INJECTION, SOLUTION
Manufacturer: TURK ILAC VE SERUM SANAYI
Category: prescription | Type: HUMAN PRESCRIPTION DRUG LABEL
Date: 20250402

ACTIVE INGREDIENTS: SODIUM LACTATE 310 mg/100 mL; SODIUM CHLORIDE 600 mg/100 mL; POTASSIUM CHLORIDE 20 mg/100 mL; CALCIUM CHLORIDE 20 mg/100 mL

DESCRIPTION

NAME OF HUMAN MEDICAL PRODUCT TURKFLEKS LACTATED RINGER'S SOLUTION

QUALITATIVE AND QUANTITATIVE COMPOSITION

Active ingredients: Each 100 ml solution: Sodium lactate (50%) 310 mg (620 mg) Sodium chloride 600 mg Potassium chloride 30 mg Calcium chloride dihydrate 20 mg

Electrolyte concentrations in solution mEq/L (mmol/L): - Sodium: 130 (130) - Calcium: 3 (1.5) - Chloride: 109 (109) - Potassium: 4 (4) - Lactate: 28 (28)

Excipients: Water

Sterile solution for intravenous infusion and sterile irrigation. Clear solution with no visible particles. 272 mOsm/L (approximately) pH: 6.0 – 7.5

CLINICAL PHARMACOLOGY

Therapeutic indications - In cases where electrolyte therapy at isotonic concentration is sufficient to restore extracellular fluid volume and electrolyte balance or to replace extracellular fluid losses.

- In short-term volume replacement therapy in cases of hypovolemia or hypotension (alone or in combination with a colloidal solution). - In the regulation or maintenance of acid-base balance and/or in the treatment of mild to moderate metabolic acidosis (excluding lactic acidosis).

Dosage and method of administration Dosage / frequency and duration of administration: In intravenous infusion administration: The dose to be administered, infusion rate and duration of administration should be adjusted by the physician according to the indication for which the solution is used, the patient's age, body weight and clinical condition, the treatment administered to the patient with the solution, and the clinical and laboratory response to the treatment. In general, in order to provide normal blood volume in blood losses, TURKFLEKS LACTATED RINGER is required 3-5 times the amount of blood lost. In general, doses of 500 - 3000 mL per day are recommended for adults and 20 - 100 mL per kg of body weight per day for children. The rate of administration in adults is usually 40 mL per kg of body weight per day. Method of administration: Application is performed intravenously with sterile apyrogen sets.

Additional information regarding special populations: Renal/Liver failure: Since there is no study specifically conducted for these populations, there is no special dosage recommendation for this patient group. Turkflex Lactated Ringer may not show its alkalizing effect since lactate metabolism may be impaired in patients with hepatic failure. Pediatric population: The effectiveness and safe use of lactated Ringer's solutions in children have not been investigated with appropriate and well-controlled studies; however, there is information in the medical literature indicating the use of electrolyte solutions in the pediatric population. Lactated solutions should be administered with special care to newborns and infants younger than 6 months.

In the pediatric population, infusion rates are 5 mL/kg per hour on average, but they vary according to age as follows: • 6-8 mL/kg/hour in infants older than 1 month • 4-6 mL/kg/hour in children aged 1-2 years • 2-4 mL/kg/hour in children older than 2 years It is recommended to administer an average dose of 3.4 mL/kg/burn rate in the first 24 hours and 6.3 mL/kg/burn rate on the second day in children with burns. The average dose in children with severe head trauma is 2,850 mL/m2. During surgery or when necessary, the infusion may be faster or the total volume administered may be greater. Geriatric population: When determining the type of infusion solution and the rate and volume of administration in geriatric patients, it should be taken into account that heart, kidney, liver diseases and other diseases and drug use are more common in this age group.

CONTRAINDICATIONS

• Patients with known hypersensitivity to sodium lactate • Extracellular hyperhydration or hypervolemia • Severe renal failure (with oliguria/anuria) • Decompensated heart failure • Hyperkalemia • Hypercalcemia • Metabolic alkalosis • Cirrhosis with ascites • Severe metabolic acidosis • Conditions with increased lactate levels (hyperlactatemia), including conditions in which lactate utilization is impaired, such as lactic acidosis or severe hepatic failure • Use with digitalis therapy (See 4.5. Interactions with other medicinal products and other forms of interaction) • In newborn infants under 28 days of age, the use of TURKFLEKS LACTATED RINGER, like other calcium-containing solutions, with ceftriaxone is contraindicated, even if administered through separate infusion lines (due to fatal ceftriaxone calcium salt precipitation in the newborn's bloodstream).
For the use of TURKFLEKS LACTATED RINGER with ceftriaxone in patients older than 28 days, see section '4.4. Special warnings and precautions for use'.

WARNINGS AND PRECAUTIONS

Special warnings and precautions for use Hypersensitivity reactions If any signs or symptoms suggestive of a hypersensitivity reaction occur during administration, the infusion should be stopped immediately. Appropriate therapeutic interventions should be implemented as clinically indicated. Incompatibilities Ceftriaxone: In patients older than 28 days, including adults, ceftriaxone should not be used simultaneously with calcium-containing solutions, including TURKFLEKS LACTATED RINGER, through the same infusion line. If the same administration set is to be used for successive applications, the set should be thoroughly rinsed with compatible solutions before administration. For the use of TURKFLEKS LACTATED RINGER with ceftriaxone in newborn infants younger than 28 days, see “4.3. Contraindications”. Electrolyte balance Hypernatremia: In cases of hypernatremia, TURKFLEKS LACTATED RINGER should only be used after careful investigation of the cause of the underlying disease and in cases where alternative intravenous fluid treatments cannot be applied. In such cases, it is recommended to monitor plasma sodium levels and plasma volume and apply.

TURKFLEKS LACTATED RINGER should be applied with special care in cases that increase the tendency to hypernatremia (such as adrenocortical insufficiency, diabetes insipidus or widespread tissue damage) and in patients with cardiac disease. Hyperchloremia: In cases of hyperchloremia, TURKFLEKS LACTATED RINGER should be used only after the cause of the underlying disease has been carefully investigated and in cases where alternative intravenous fluid treatments cannot be applied. In such cases, it is recommended to apply by monitoring plasma chloride levels and plasma acid-base balance.

TURKFLEKS LACTATED RINGER should be administered with special care in conditions that increase the tendency to hyperchloremia (such as renal failure and renal tubular acidosis, diabetes insipidus), in patients who have undergone urinary diversion or who are taking certain diuretics (such as carbonic anhydrase inhibitors such as acetazolamide) or steroids (androgens, estrogens, corticosteroids), and in patients with severe dehydration. Use in patients with potassium deficiency: Although the amount of potassium in the composition of TURKFLEKS LACTATED RINGER is similar to that of plasma, the solution should not be used for this purpose, as it is not at a level that will have a beneficial effect in cases of severe potassium deficiency. Use in patients at risk of hyperkalemia: TURKFLEKS LACTATED RINGER should be applied with special care in conditions that increase the tendency to hyperkalemia (such as severe renal failure or adrenocortical insufficiency, acute dehydration or widespread tissue damage or burns) and in patients with cardiac disease. It is recommended to closely monitor plasma potassium levels in patients at risk of hyperkalemia. Use in patients at risk of hypercalcemia: Calcium chloride is an irritant; therefore, care should be taken not to leak solution out of the vein when administered intravenously or intramuscularly.

Solutions containing calcium salts should be used with caution in patients with impaired renal function or high vitamin D levels, such as sarcoidosis. In addition, it should be avoided in patients with a history of calcium stones in the kidneys. Fluid balance / kidney functions Use in patients with impaired renal function: TURKFLEKS LACTATED RINGER should be administered with special care to patients with impaired renal function. In such patients, administration of TURKFLEKS LACTATED RINGER may cause sodium and/or potassium accumulation. Use in patients at risk of fluid and/or solute overload and electrolyte disturbances: Depending on the volume administered and the rate of administration, intravenous administration of TURKFLEKS LACTATED RINGER may cause the following conditions: - Fluid and/or solute overload leading to overhydration and congestive conditions (including pulmonary congestion and edema).

- Clinically relevant electrolyte disturbances and acid-base imbalance. During long-term parenteral administration, the patient's clinical condition and laboratory parameters should be monitored at regular intervals whenever the patient's condition or the rate of intravenous fluid administration requires it. High-volume infusions should be administered with special monitoring in patients with heart or lung failure. Use in patients with hypervolemia, overhydration or conditions that lead to sodium retention and edema: TURKFLEKS LACTATED RINGER should be administered with special caution in patients with hypervolemia or overhydration. TURKFLEKS LACTATED RINGER should be administered with special caution in patients with primary hyperaldosteronism, secondary hyperaldosteronism (e.g. hypertension, congestive heart failure, renal artery stenosis or nephrosclerosis) or conditions that may lead to sodium retention, fluid overload and edema such as preeclampsia due to its sodium chloride content (See Section 4.5.).

Acid-base balance Use in patients at risk of alkalosis: TURKFLEKS LACTATED RINGER should be administered with special care in patients at risk of alkalosis. Since lactate is metabolized to bicarbonate, the solution may cause metabolic alkalosis in such patients or may aggravate an existing metabolic alkalosis. Although convulsions may be induced in lactate-induced alkalosis, this is not a common condition. Other warnings Application with citrate anticoagulated/stored blood: Due to the calcium it contains, it is not recommended to add TURKFLEKS LACTATED RINGER to citrate anticoagulated/stored blood, to citrate anticoagulated/stored blood, to administer simultaneously or to administer together from the same infusion system. Use in patients with type 2 diabetes: Lactate is a substrate for gluconeogenesis. This should be taken into consideration when using TURKFLEKS LACTATED RINGER in patients with type 2 diabetes.

Warnings regarding administration: Addition of additional drugs according to the procedure or failure to perform the application with appropriate techniques may lead to fever reactions due to pyrogen contamination. In such a case, the infusion should be stopped immediately. Please see Sections 6.2 and 6.6 regarding incompatibilities of the solution and addition of additional drugs to the product. During long-term parenteral therapy, the patient should be given appropriate nutritional support.

OTHER SAFETY INFORMATION

Interactions related to the sodium content of the solution: - In patients using drugs such as corticosteroids that may increase the risk of sodium and fluid overload (with edema and hypertension), TURKFLEKS LACTATED RINGER is recommended to be administered with caution. Interactions related to the potassium content of the solution: Since TURKFLEKS LACTATED RINGER contains potassium, it is recommended to be administered with caution when used with the following drugs known to cause or increase the risk of hyperkalemia: - Potassium-sparing diuretics (amiloride, spironolactone, triamterene, alone or in combination). - Angiotensin converting enzyme inhibitors and angiotensin II receptor antagonists. - Tacrolimus, cyclosporine. In patients receiving such drugs, especially in cases of severe renal impairment, the administration of potassium may result in a severe and potentially fatal hyperkalemia.

Interactions related to the calcium contained in the solution: Administering calcium may increase the effects of digitalis and may cause serious or potentially fatal arrhythmias in the heart. Therefore, in patients receiving treatment with digitalis group drugs, large volumes and rapid infusion of the solution is not recommended. It is recommended that TURKFLEKS LACTATED RINGER be administered with caution if it is to be used with thiazide group diuretics or vitamin D, which may increase the risk of hypercalcemia.

Bisphosphonates, fluoride, some fluoroquinolones and tetracyclines have reduced absorption (reduced bioavailability) when administered with calcium. Interactions related to the lactate contained in the solution (metabolized to bicarbonate): It is recommended that TURKFLEKS LACTATED RINGER be administered with caution if used with drugs whose renal elimination is pH-dependent: Since bicarbonate formed as a result of lactate metabolism alkalinizes the urine, TURKFLEKS LACTATED RINGER may affect the elimination of such drugs: - Since bicarbonate formed as a result of lactate metabolism alkalinizes the urine, renal excretion of acidic drugs such as salicylates, barbiturates and lithium increases. - The renal elimination of alkaline drugs such as sympathomimetic drugs (e.g. ephedrine, pseudoephedrine) and stimulant drugs (e.g. dexamphetamine sulfate, fenfluramine hydrochloride) is slowed down.

PREGNANCY

General advice Pregnancy category: C. Women with childbearing potential/Birth control (Contraception) TURKFLEKS LACTATED RINGER can be used safely in women with childbearing potential as long as electrolyte and fluid balance is kept under control. Interaction with birth control pills is not known. Pregnancy TURKFLEKS LACTATED RINGER can be used safely in women during pregnancy as long as electrolyte and fluid balance is kept under control. It should be kept in mind that calcium passes through the placenta. If any drug is to be added to the solution, the properties of the drug used and the use of this drug during pregnancy should be evaluated separately.

LACTATION

As long as the electrolyte and fluid balance is kept under control, TURKFLEKS LACTATED RINGER can be used safely in lactating women. It should be kept in mind that calcium passes through the placenta and is distributed into breast milk. If any drug is to be added to the solution, the characteristics of the drug used and the use of this drug during lactation should be evaluated separately.

FEMALES AND MALES OF REPRODUCTIVE POTENTIAL

It has no known effects.

ADVERSE REACTIONS

Listed below are adverse reactions reported spontaneously in post-marketing experience. Adverse reactions are listed according to the MedDRA System Organ Classification. The following terminology is used when reporting frequency: Very common (≥1/10); common (≥1/100 to <1/10); uncommon (≥1/1,000 to <1/100); rare (≥1/10,000 to <1/1,000), very rare, including isolated reports (<1/10,000); not known (cannot be estimated from available data). Immune system disorders Not known: Hypersensitivity/infusion reactions (including anaphylactic/anaphylactoid reactions) with one or more of the following symptoms: angioedema, chest pain, chest discomfort, decreased heart rate, tachycardia, decreased blood pressure, respiratory distress, bronchospasm, dyspnea, cough, urticaria, rash, pruritus, erythema, flushing of the face and/or neck, throat irritation, paresthesia, hypoesthesia of the mouth, dysgeusia, nausea, anxiety, pyrexia, and headache.

Metabolism and nutritional disorders Not known: Hyperkalemia. General disorders and administration site conditions Not known: Infusion site reactions, which may be seen with one or more of the following symptoms: Phelbitis, inflammation at the infusion site, swelling, rash, pruritus, erythema, pain and burning sensation. The following is a list of adverse reactions that have been spontaneously reported during the use of other sodium lactate-containing solutions: Immune system disorders Not known: Hypersensitivity reactions: Laryngeal edema (Quincke edema), skin swelling, nasal congestion, sneezing/sneezing.

Metabolism and nutritional disorders Unknown: Electrolyte disorders. Psychiatric disorders Unknown: Anxiety. Vascular disorders Unknown: Hypervolemia. General disorders and administration site conditions Unknown: Other infusion site reactions: infusion site infection, extravasation, infusion site anesthesia (numbness). Reporting of suspected adverse reactions Reporting of suspected adverse reactions to drugs after licensing is of great importance. Reporting allows continuous monitoring of the benefit/risk balance of the drug. Healthcare professionals should report any suspected adverse reactions to the Turkish Pharmacovigilance Center (TÜFAM) (www.titck.gov.tr; e-mail: tufam@titck.gov.tr; tel: 0 800 314 00 08; fax: 0 312 218 35 99).

OVERDOSAGE

Excessive doses or too rapid administration of TURKFLEKS LACTATED RINGER may lead to water and sodium overload, which may lead to the risk of edema (peripheral and/or pulmonary edema), especially in cases where sodium excretion from the kidneys is impaired. In this case, renal dialysis treatment may be required. Excessive administration of potassium may lead to hyperkalemia, especially in patients with renal failure. Symptoms of hyperkalemia include paresthesia in the extremities, muscle weakness, paralysis, cardiac arrhythmias, heart block, cardiac arrest and mental confusion. Excessive calcium administration may cause hypercalcemia. Symptoms of hypercalcemia include anorexia, nausea, vomiting, constipation, abdominal pain, muscle weakness, mental disorders, polydipsia, polyuria, nephrocalcinosis, renal stone formation and, in more severe cases, cardiac arrhythmias and coma. Too rapid infusion of calcium salts can cause a chalky taste in the mouth, flushing, especially of the face, and peripheral vasodilation, as well as many other symptoms of hypercalcemia. Mild asymptomatic hypercalcemia is caused by calcium and D
It is corrected by stopping the administration of drugs such as vitamin. If hypercalcemia is severe, treatments such as loop diuretics, hemodialysis, calcitonin, bisphosphonate and trisodium edetate should be started urgently. Sodium lactate overdose can lead to metabolic alkalosis. Metabolic alkalosis may be accompanied by hypokalemia. Symptoms include mood changes, weakness, breathlessness, muscle weakness and irregular heartbeat. Hypertonicity, twitching and tetany can be seen in muscles, especially in hypocalcemic patients. Treatment of metabolic alkalosis due to bicarbonate overdose mainly consists of appropriate correction of fluid and electrolyte balance. Complementation of calcium, chloride and potassium deficiencies is especially important. If the overdose is due to drugs added to the solution, the signs and symptoms of the overdose depend on the properties of the added drug. If the dose is accidentally exceeded during treatment, the administration should be stopped and the patient should be monitored for signs and symptoms related to the drug administered. If necessary, symptomatic and supportive treatments should be applied.

PHARMACODYNAMICS

Pharmacotherapeutic group: Intravenous solutions / Solutions affecting electrolyte balance ATC code: B05BB01 TURKFLEKS LACTATED RINGER is an isotonic electrolyte solution. The composition and concentration of electrolytes in TURKFLEKS LACTATED RINGER are designed to be similar to those of electrolytes in plasma. The pharmacological properties of TURKFLEKS LACTATED RINGER consist of the pharmacological properties of its components (sodium, potassium, calcium, chloride and lactate). The main effect of TURKFLEKS LACTATED RINGER is the expansion of fluid in the extracellular compartment, including interstitial and intravascular fluids. Lactate ions are metabolized to bicarbonate, mainly in the liver, creating an alkalizing effect on the plasma. In healthy volunteers given lactated Ringer's solution, changes in central venous pressure were associated with atrial natriuretic peptide secretion.

Lactated Ringer's solutions applied to healthy volunteers decreased serum osmolality, increased blood pH and provided the first urination in a shorter time compared to normal saline application. No significant changes were observed in glucagon, epinephrine, blood glucose and insulin levels in aortic surgery patients treated with Lactated Ringer's solutions. When a drug is added to TURKFLEKS LACTATED RINGER, the pharmacodynamic properties of the resulting solution depend on the properties of the added drug.

PHARMACOKINETICS

The pharmacokinetic properties of TURKFLEKS LACTATED RINGER consist of the pharmacokinetic properties of its components (sodium, potassium, calcium, chloride and lactate).

Infusion of Lactated Ringer's solutions in hemodynamically stable adults does not cause an increase in circulating lactate levels. The pharmacokinetics of D-lactate and L-lactate are similar.
Absorption:
Active substances in intravenously administered drugs reach maximum plasma concentrations immediately after administration.
Distribution:
The half-life after injection of radioactively labeled sodium (24Na) is 11-13 days for 99% of the injected sodium and one year for the remaining 1%. Distribution varies according to the tissues: fast in muscle, liver, kidney, cartilage and skin, slow in erythrocytes and neurons, and very slow in bone.
Potassium in the extracellular fluid enters the cell by active transport until it reaches 40 times its concentration outside the cell. Glucose, insulin, and oxygen facilitate the entry of potassium into the cell. In healthy adults, plasma potassium concentration is in the range of 3.5-5 mEq/l. In newborns, plasma levels can reach up to 7.7 mEq/l. However, since plasma potassium levels do not fully reflect intracellular potassium levels, cellular hypokalemia may occur even when plasma levels are normal. Changes in pH in the extracellular fluid also cause changes in plasma potassium concentration. A 0.1 unit change in plasma pH causes an inversely proportional change in plasma potassium concentration of 0.6 mEq/l.

Chloride is normally found in low amounts in bone tissue and in high amounts in some components of connective tissue, such as collagen tissue. It is also found in high concentrations in erythrocytes and gastric mucosa. The levels of chloride, the main anion of extracellular fluid, in the body are closely related to changes in sodium concentration. Abnormalities in sodium metabolism usually result in changes in chloride concentration.

Calcium is an important cation for the continuation of life both intracellularly and extracellularly. Depending on the requirement, it either remains in the plasma or distributes to the tissues. Calcium also passes into the placenta and breast milk.
Lactate is converted to bicarbonate by oxidation in serum. Lactate distributed to the liver is metabolized by gluconeogenesis in the liver and converted to bicarbonate.
Biotransformation:
Sodium, potassium, calcium and chloride do not undergo any biotransformation. Depending on the requirement, they are either distributed to body fluids and tissues or eliminated.
Lactate is metabolized by both oxidation and gluconeogenesis, especially in the liver, to form bicarbonate within approximately 1-2 hours.

Elimination:
Sodium is mainly excreted renally, but most of it is also reabsorbed renally. A small amount of sodium is excreted in feces and sweat. Excretion through the skin is unimportant unless there is excessive sweating.
Closely following sodium metabolism, chloride ion is also excreted mainly in urine. Chloride reabsorption from the kidneys generally follows sodium reabsorption. In addition, some amount is also excreted through sweat.
80-90% of potassium is excreted by the kidneys. The rest is excreted in feces and a very small amount is excreted through sweat. Potassium is filtered in the glomeruli, reabsorbed in the proximal tubules and secreted in the distal tubules by Na-K exchange. Tubular secretion of potassium is also affected by hydrogen ion exchange, acid-base balance and adrenal hormones.
Calcium is excreted mainly in feces; small amounts are also excreted by sweat glands.
Linearity/non-linearity: Lactated Ringer's solutions exhibit linear pharmacokinetics over the recommended dosage range.

OTHER SAFETY INFORMATION

SPECIFICATIONS
Incompatibilities

Ceftriaxone should not be mixed with calcium-containing solutions, including TURKFLEKS LACTATED RINGER. Please see Sections 4.3 and 4.4 on this subject.
As with all solutions administered parenterally, additional drugs added to the solution may be incompatible. The compatibility of the drug to be added to the solution with TURKFLEKS LACTATED RINGER and its bag should be evaluated before adding the drug. Incompatibility can be understood by looking at whether there is a color change and/or precipitation, insoluble compounds or crystallization after the drug is added.

For drug addition, the Summary of Product Characteristics of the drug to be added and the relevant literature should be consulted.
Before adding any substance or drug to the solution, it should be confirmed that TURKFLEKS LACTATED RINGER is soluble and stable at its pH (pH: 6-7.5).

Adding drugs to TURKFLEKS LACTATED RINGER should be done with aseptic technique. The solution should be mixed thoroughly after adding drugs. Solutions containing additional drugs should not be stored.

As a guide, some of the drugs that are incompatible with TURKFLEKS LACTATED RINGER are given below (not an exhaustive list showing all incompatibilities):
Some of the drugs that are incompatible with TURKFLEKS LACTATED RINGER:
- Amino caproic acid
- Amphotericin B
- Metaraminol tartrate
- Cefamandole
- Ceftriaxone
- Cortisone acetate

-Diethylstilbestrol
-Etamivan
-Ethyl alcohol
-Phosphate and carbonate containing solutions
-Oxytetracycline
-Thiopental sodium
-Versenate disodium
Some of the drugs that are partially incompatible with TURKFLEKS LACTATED RINGER:
-Tetracycline is stable for 12 hours.
-Ampicillin sodium concentrations of 2% - 3% are stable for 4 hours, and concentrations higher than 3% are stable for 1 hour.
-Minocycline is stable for 12 hours.
-Doxycycline is stable for 6 hours.
Additional drugs that are known or determined to be incompatible should not be used.

Shelf life
36 months. Shelf life during use: In microbiological terms, if the preparation for application is not carried out under controlled and validated aseptic conditions, it should be used immediately after preparation. In cases where it is not used immediately, the person who adds/dilutes the drug is responsible for determining the storage conditions and duration. 6.4. Special precautions for storage There are no special storage conditions, it should be stored at room temperature below 25 ° C. 6.5. Nature and content of packaging In 500 and 1000 ml Turkfleks (polypropylene) bags. The product has two forms: with and without a set.
Send feedback
Side panels
History
Saved

DISPOSAL AND WASTE HANDLING

Unused products or waste materials must be disposed of in accordance with the "Medical Waste Control Regulation" and "Packaging Waste Control Regulation". They are for single use. Partially used solutions should not be stored. Partially used bags should not be reconnected to systems applied to the patient.

The solution should be checked before use.

The application is made intravenously with sterile apyrogen sets (intra-articularly or directly by pouring if used as an irrigation solution).
Only clear, particle-free products with intact packaging should be used.
The application should be started as soon as possible after the application set is attached to the product.
To prevent air embolism that may occur due to residual air in the bag, serial connections should not be made with other infusion fluids.
The solution should be applied using aseptic technique through a sterile application set. In order to prevent air from entering the system, the liquid should be passed through the application set before use.
Additional drugs can be added with a needle under aseptic conditions before and during infusion. The isotonicity of the final product formed should be determined before parenteral administration.
The drug added to the patient should be completely mixed with the solution before administration. Solutions containing additional drugs should be used immediately after adding the drug; they should not be stored for later use.
Adding additional drugs to the solution or incorrect application technique may cause a fever reaction due to pyrogen contamination of the product. In case of an adverse reaction, the infusion should be stopped immediately.

To open:
1. Check the integrity of the outer packaging and whether there is any leakage; do not use if the packaging is damaged.
2. Tear open the protective outer packaging.
3. Check that the bag inside the protective packaging is intact by squeezing it.
4. Check that the solution in the bag is clear and does not contain foreign matter.
Preparations for application:
1. Hang the bag.
2. Remove the protective cap from the application tip.
3. Firmly insert the spike of the application set into the application tip. The instructions for use of the set should be followed in order for the solution to be passed through the set and applied to the patient.

Adding additional drugs:
Caution: As with all parenteral solutions, all substances to be added to the product must be compatible with the product. If the product is to be added, compatibility should be checked in the final mixture before administration to the patient.
Adding drugs before application
1. Disinfect the drug application tip.
2. The drug to be added is applied from the drug application tip with a syringe with a 19-22 gauge needle.
3. Mix the solution and the drug added thoroughly (for concentrated drugs such as potassium chloride, mix by gently tapping the application outlet of the bag while it is in the upright position).
Caution: Bags with additional drugs applied should not be stored.
Adding drugs during application
1. Close the clamp of the set.
2. Disinfect the drug application tip.
3. The drug to be added is applied from the drug application tip with a syringe with a 19-22 gauge needle.
4. Remove from the solution hanger and turn upside down. In this position, the application outlet and injection inlet of the bag are gently tapped to mix the solution and additional medication. 5. The clamp is opened by returning the bag to its original position and the application is continued.
Send feedback
Side panels
History
Saved

HEALTH CARE PROVIDER LETTER

April 02, 2025

Subject: Temporary importation of Turkfleks Lactated Ringer’s Injection from Turk Ilac located in Ankara-TURKEY to address drug shortages per

https://dps.fda.gov/drugshortages/activeingredient/lactated-ringers-injection

To prevent a shortage of large volume parenteral fluid drug products, Turk Ilac ve Serum Sanayi is coordinating with the U.S. Food and Drug Administration (FDA) to temporarily import Turkfleks Lactated Ringer’s Injection (500ml and 1000 ml) from Turk Ilac ve Serum Sanayi manufacturing facility located in Ankara/TURKEY. FDA has not approved these products manufactured by Turk Ilac ve Serum Sanayi.

Effective immediately, and during this temporary period, Turk Ilac ve Serum Sanayi will offer the following imported product from Turk Ilac ve Serum Sanayi facility located in Ankara/TURKEY:

Product Name and Description | Volume | Bags per Box | NDC Code
Turkfleks Lactated Ringer’s Injection | 500ml | 20 | 85160-500-10
Turkfleks Lactated Ringer’s Injection | 1000ml | 20 | 85160-500-20

Please note the following:

- Upon receiving Submission Acceptance Turk Ilac ve Serum Sanayi will have bag labels written in both Turkish and English.
- The bag labels will contain the active pharmaceutical ingredient, concentration, volume, and NDC code in English.
- The imported products' administration port system is fully compatible with sets marketed in the United States.
- The imported products use a carton box that is taped closed. To avoid damage to the solution container, take care not to use sharp instruments to open the box.
- The imported products do not contain barcodes on the unit label. Alternative procedures should be followed to ensure that the correct drug product is being used in all systems and processes and administered to individual patients. For example, institutions should consider manually inputting the product into their systems and confirm that barcode systems do not provide incorrect information when the product is scanned.
- 0.9% Isotonic Sodium Chloride Injection is available only by prescription in the United States. However, the imported products do not have the statement "Rx only" on the labeling.
- USE A NEW BAG IF PARTICULATES ARE VISIBLE OR IF THE IV BAG CONTAINS A LEAK.

Additional key differences in the labeling between the FDA-approved product and the imported products are stated in the product comparison table at the end of this letter as follows:

Table 1. Key differences between FDA-approved and Turkfleks Lactated Ringer’s Injection

Table 2. Label images of FDA-approved and Turkfleks Lactated Ringer’s Injection

Reporting Adverse Events or Product Quality Issues

To report adverse events associated with these imported products, please use the contact us at info@turkilac.com.tr.

Adverse events or quality problems experienced with the use of these imported products may also be reported to the FDA's MedWatch Adverse Event Reporting program either online, by regular mail or by fax:

- Complete and submit the report Online: www.fda.gov/medwatch/report.htm
- Regular mail or Fax: Download form www.fda.gov/MedWatch/getforms.htm

or call 1-800332-1088 to request a reporting form, then complete and return to the address on the preaddressed form or submit by fax to 1-800-FDA-0178 (1-800-332-0178).

Sincerely,

Mehmet Berat Battal

Table 1: Key Differences between FDA Approved product and Turkfleks Lactated Ringer’s Injection

 | FDA- Approved Product | Turkfleks Import from Turkey
Product Name | Lactated Ringer’s Injection USP | Turkfleks Lactated Ringer’s Injection
Indications | This solution is indicated for use in adults and pediatric patients as a source of electrolytes and water for hydration. | - In cases where electrolyte therapy at isotonic concentration is sufficient for the correction of extracellular fluid volume and electrolyte balance or for the replacement of extracellular fluid losses.; 2 / 18; - In short-term volume replacement therapy in cases of hypovolemia or hypotension (alone or in combination with a colloid solution).; - In the regulation or maintenance of acid-base balance and/or in the treatment of mild to moderate metabolic acidosis (except lactic acidosis).
Active Ingredients | Per 100 ml solution:; Sodium lactate (50%) 310 mg (620 mg) Sodium chloride 600 mg; Potassium chloride 30 mg Calcium chloride dihydrate 20 mg; Electrolyte concentrations in solution mEq/L (mmol/L):; - Sodium: 130 (130); - Calcium: 3 (1.5); - Chloride: 109 (109); - Potassium: 4 (4); - Lactate: 28 (28) | Per 100 ml solution:; Sodium lactate (50%) 310 mg (620 mg) Sodium chloride 600 mg; Potassium chloride 30 mg Calcium chloride dihydrate 20 mg; Electrolyte concentrations in solution mEq/L (mmol/L):; - Sodium: 130 (130); - Calcium: 3 (1.5); - Chloride: 109 (109); - Potassium: 4 (4); - Lactate: 28 (28)
Additional Information | pH is 6.2 (4.5-7.0) Osmolarity 275 mOsm/L (calc) | pH is 6.0-7.5 Osmolarity 272 mOsm/L (calc)
Store Conditions | Store at room temperature 25C/77F | Store at below 30C
Container Type | ethylene and propylene | Polypropylene

Table 2: Label Images of FDA-approved and Turkfleks Lactated Ringer’s Injection

FDA-approved Product | Turkfleks Lactated Ringer’s Injection